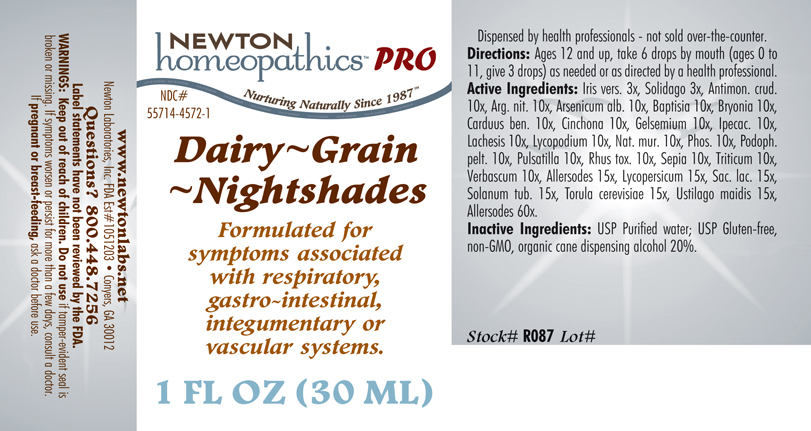 DRUG LABEL: Dairy - Grain - Nightshades 
NDC: 55714-4572 | Form: LIQUID
Manufacturer: Newton Laboratories, Inc.
Category: homeopathic | Type: HUMAN PRESCRIPTION DRUG LABEL
Date: 20110601

ACTIVE INGREDIENTS: Cow Milk 60 [hp_X]/1 mL; Skim Milk 60 [hp_X]/1 mL; Cow Milk Fat 60 [hp_X]/1 mL; Casein, Lactococcus Lactis Cultured, Aged 60 [hp_X]/1 mL; Casein, Lactococcus Lactis Cultured, Penicillium Roqueforti Cultured, Aged 60 [hp_X]/1 mL; Casein, Lactococcus Lactis Cultured, Penicillium Camemberti Cultured, Aged 60 [hp_X]/1 mL; Barley 60 [hp_X]/1 mL; Corn 60 [hp_X]/1 mL; Wheat Gluten 60 [hp_X]/1 mL; Oat 60 [hp_X]/1 mL; White Rice 60 [hp_X]/1 mL; Rye 60 [hp_X]/1 mL; Wheat 60 [hp_X]/1 mL; Atropa Belladonna 15 [hp_X]/1 mL; Capsicum 15 [hp_X]/1 mL; Solanum Dulcamara Top 15 [hp_X]/1 mL; Hyoscyamus Niger 15 [hp_X]/1 mL; Solanum Nigrum Whole 15 [hp_X]/1 mL; Datura Stramonium 15 [hp_X]/1 mL; Tobacco Leaf 15 [hp_X]/1 mL; Solanum Lycopersicum 15 [hp_X]/1 mL; Lactose 15 [hp_X]/1 mL; Solanum Tuberosum 15 [hp_X]/1 mL; Saccharomyces Cerevisiae 15 [hp_X]/1 mL; Ustilago Maydis 15 [hp_X]/1 mL; Antimony Trisulfide 10 [hp_X]/1 mL; Silver Nitrate 10 [hp_X]/1 mL; Arsenic Trioxide 10 [hp_X]/1 mL; Baptisia Tinctoria Root 10 [hp_X]/1 mL; Bryonia Alba Root 10 [hp_X]/1 mL; Centaurea Benedicta 10 [hp_X]/1 mL; Cinchona Officinalis Bark 10 [hp_X]/1 mL; Gelsemium Sempervirens Root 10 [hp_X]/1 mL; Ipecac 10 [hp_X]/1 mL; Lachesis Muta Venom 10 [hp_X]/1 mL; Sodium Chloride 10 [hp_X]/1 mL; Phosphorus 10 [hp_X]/1 mL; Podophyllum 10 [hp_X]/1 mL; Pulsatilla Vulgaris 10 [hp_X]/1 mL; Toxicodendron Pubescens Leaf 10 [hp_X]/1 mL; Sepia Officinalis Juice 10 [hp_X]/1 mL; Elymus Repens Root 10 [hp_X]/1 mL; Verbascum Thapsus 10 [hp_X]/1 mL; Iris Versicolor Root 3 [hp_X]/1 mL; Solidago Virgaurea Flowering Top 3 [hp_X]/1 mL; Lycopodium Clavatum Spore 10 [hp_X]/1 mL
INACTIVE INGREDIENTS: Alcohol; Water

Dairy - Grain - Nightshades

INDICATIONS & USAGE SECTION

Formulated for symptoms associated with respiratory, gastro-intestinal, integumentary or vascular systems.

DOSAGE & ADMINISTRATION SECTION

Directions: Ages 12 and up, take 6 drops by mouth (ages 0 to 11, give 3 drops) as needed or as directed by a health professional.

OTC - ACTIVE INGREDIENT SECTION

Allersodes 60x, Allersodes 15x , Lycopersicum 15x, Sac. lac. 15x, Solanum tub. 15x, Torula cerevisiae 15x, Ustilago maidis 15x, Antimon. crud. 10x, Arg. nit. 10x, Arsenicum alb. 10x, Baptisia 10x, Bryonia 10x, Carduus ben. 10x, Cinchona 10x, Gelsemium 10x, Ipecac. 10x, Lachesis 10x, Lycopodium 10x, Nat. mur. 10x, Phos. 10x, Podoph. pelt.10x, Pulsatilla 10x, Rhus tox. 10x, Sepia 10x, Triticum 10x, Verbascum 10x, Iris vers. 3x, Solidago 3x.

OTC - PURPOSE SECTION

Formulated for symptoms associated with respiratory, gastro-intestinal, integumentary or vascular systems.

INACTIVE INGREDIENT SECTION

Inactive Ingredients: USP Purified water, USP Gluten-free, non-GMO, organic cane dispensing alcohol 20%.

QUESTIONS SECTION

www.newtonlabs.net Newton Laboratories, Inc. FDA Est # 1051203 - Conyers, GA 30012
Questions? 1.800.448.7256

WARNINGS SECTION

Warning: Keep out of reach of children. Do not use if tamper-evident seal is broken or missing. If symptoms worsen or persist for more than a few days, consult a doctor. If pregnant or breast-feeding, ask a doctor before use.

OTC - PREGNANCY OR BREAST FEEDING SECTION

If pregnant or breast-feeding, ask a doctor before use.

OTC - KEEP OUT OF REACH OF CHILDREN SECTION

Keep out of reach of children.